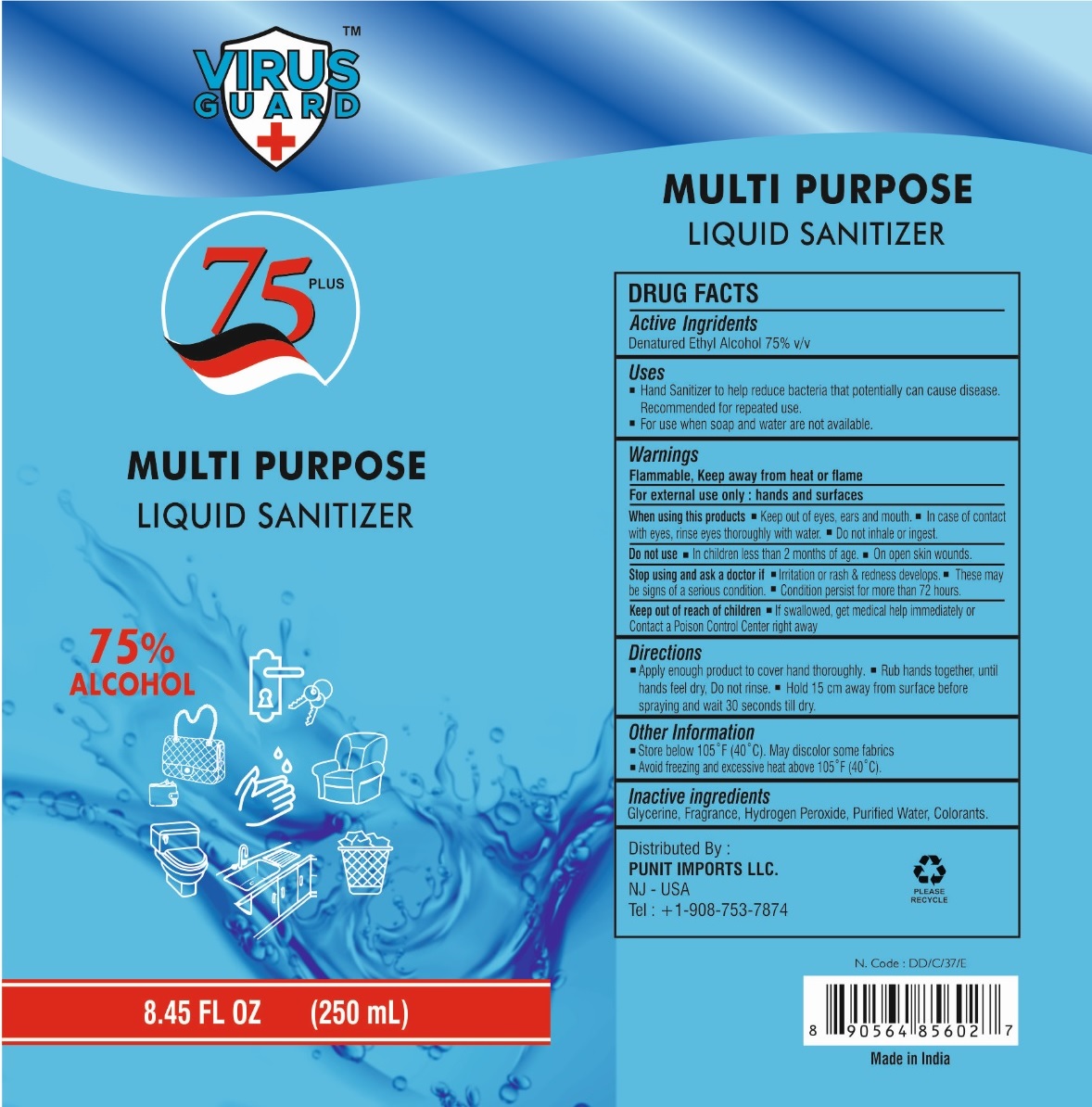 DRUG LABEL: VIRUS GUARD 75 PLUS MULTI PURPOSE SANITIZER
NDC: 77867-003 | Form: LIQUID
Manufacturer: MILAN COSMETICS PRIVATE LIMITED
Category: otc | Type: HUMAN OTC DRUG LABEL
Date: 20200718

ACTIVE INGREDIENTS: ALCOHOL 75 mL/100 mL
INACTIVE INGREDIENTS: GLYCERIN; HYDROGEN PEROXIDE; WATER

VIRUS GUARD MULTI PURPOSE LIQUID SANITIZER

Active Ingredients

Denatured Ethyl Alcohol 75% v/v

Purpose

Antiseptic

Uses

• Hand Sanitizer to help reduce bacteria that potentially can cause disease.
Recommended for repeated use.
• For use when soap and water are not available.

Warnings

Flammable, Keep away from heat or flame

For external use only : hands and surfaces

When using this products • Keep out of eyes, ears and mouth. • In case of contact with eyes, rinse eyes thoroughly with water. • Do not inhale or ingest.

Do not use • In children less than 2 months of age. • On open skin wounds.

Stop use and ask a doctor if • Irritation or rash & redness develops. • These may be signs of a serious condition. • Condition persist for more than 72 hours.

Keep out of reach of children • If swallowed, get medical help immediately or Contact a Poison Control Center right away

Directions

• Apply enough product to cover hand thoroughly. • Rub hand together, until hands feel dry, Do not rinse. • Hold 15 cm away from surface before spraying and wait 30 seconds till dry.

Other Information

• Store below 105˚F (40˚C). May discolor some fabrics

• Avoid freezing and excessive heat above 105˚F (40˚C).

Inactive ingredients

Glycerine, Fragrance, Hydrogen Peroxide, Purified Water, Colorants.

75 PLUS

75% ALCOHOL

Distributed By :

PUNIT IMPORTS LLC.

NJ - USA

Tel : +1-908-753-7874

PLEASE RECYCLE

Made in India